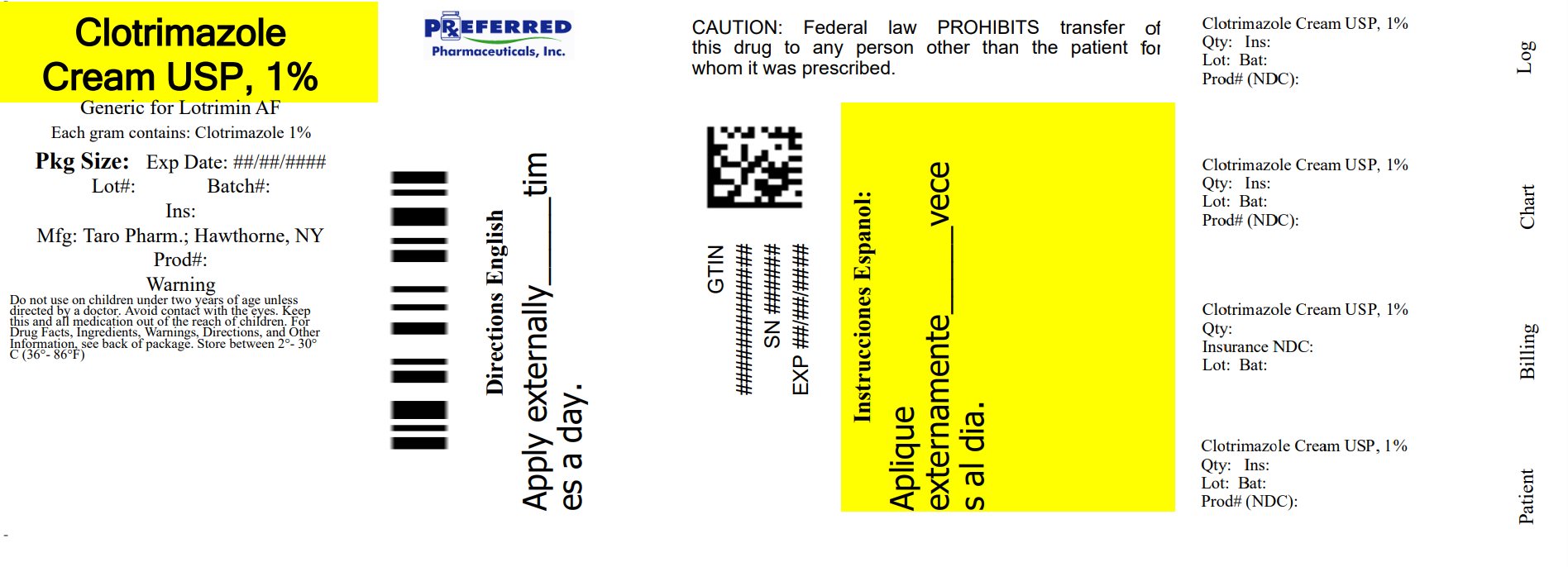 DRUG LABEL: Clotrimazole
NDC: 68788-8216 | Form: CREAM
Manufacturer: Preferred Pharmaceuticals Inc.
Category: otc | Type: HUMAN OTC DRUG LABEL
Date: 20260115

ACTIVE INGREDIENTS: Clotrimazole 1 g/100 g
INACTIVE INGREDIENTS: benzyl alcohol; cetostearyl alcohol; cetyl esters wax; polysorbate 60; water; sorbitan monostearate

Clotrimazole Cream USP,1%
Antifungal Cream

Drug Facts

Active ingredient

Clotrimazole 1%

Purpose

Antifungal

Uses

- cures most athlete's foot (tinea pedis), jock itch (tinea cruris), and ringworm (tinea corporis)
- for effective relief of
- itching
- scaling
- cracking
- burning
- redness
- soreness
- irritation
- discomfort

Warnings

For external use only

Ask a doctor before use

- on children under 2 years of age

When using this product

- avoid contact with eyes

Stop use and ask a doctor if

- irritation occurs
- there is no improvement within 4 weeks (for athlete's foot and ringworm) or within 2 weeks (for jock itch)

Keep out of reach of children. If swallowed, get medical help or contact a Poison Control Center right away.

Directions

This product is not effective on the scalp or nails.

For athlete's foot and ringworm: use daily for 4 weeks. For jock itch: use daily for 2 weeks.

- clean the affected area and dry thoroughly
- apply a thin layer of the product over affected area twice daily (morning and night) or as directed by a doctor
- supervise children in the use of this product

For athlete's foot: pay special attention to spaces between the toes; wear well-fitting, ventilated shoes; change shoes and socks at least once daily

Other information

- To open: unscrew cap, use the pointed end of cap to puncture seal.
- store between 2°- 30°C (36° - 86°F)
- see carton or tube crimp for lot number and expiration date

Inactive ingredients

benzyl alcohol (1%), cetostearyl alcohol, cetyl esters wax, 2-octyldodecanol, polysorbate 60, purified water, sorbitan monostearate

Questions?

Call 1-866-923-4914

Distributed by:
Taro Pharmaceuticals
U.S.A., Inc.
Hawthorne, NY 10532

Relabeled By: Preferred Pharmaceuticals Inc.

PRINCIPAL DISPLAY PANEL - 30 g Carton

Cures Most Athlete's Foot

Athlete's Foot
Cream
Clotrimazole Cream USP,1%
Antifungal Cream

Antifungal Cream

NDC 68788-8216-3

Relabeled By: Preferred Pharmaceuticals Inc.